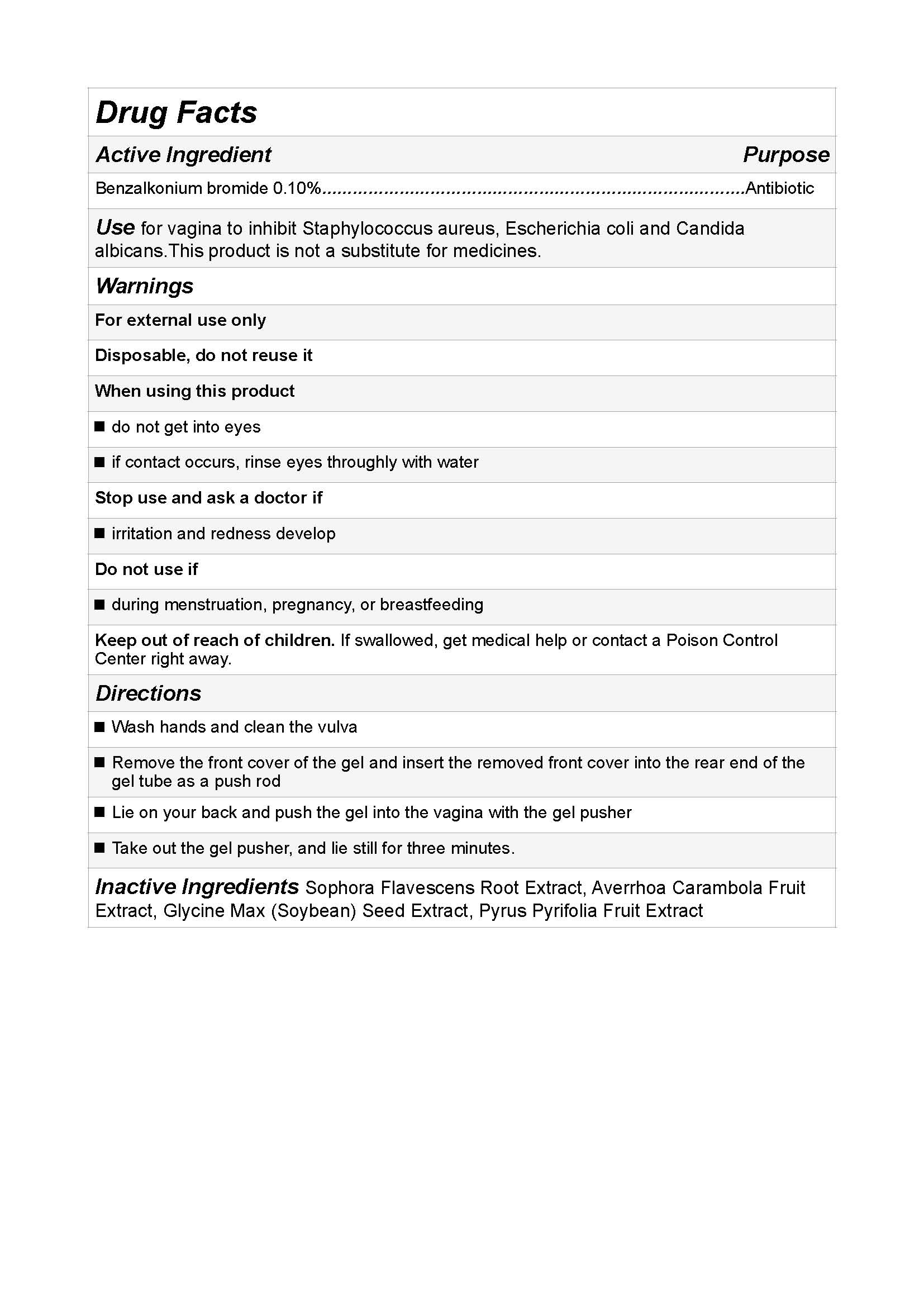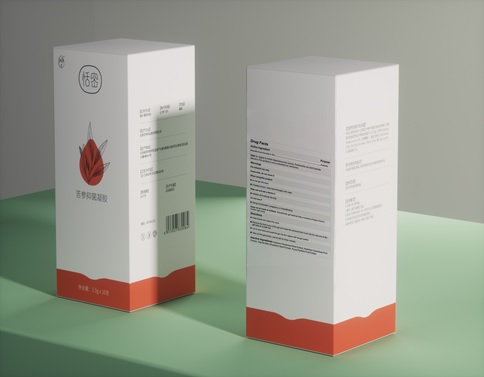 DRUG LABEL: Female Intimate Hygiene Antibacterial Gels
NDC: 81983-101 | Form: GEL
Manufacturer: ShenZhen MengTi Biotechnology Co.Ltd
Category: otc | Type: HUMAN OTC DRUG LABEL
Date: 20210607

ACTIVE INGREDIENTS: BENZALKONIUM BROMIDE 0.1 g/100 g
INACTIVE INGREDIENTS: NASHIPATI; SOPHORA FLAVESCENS WHOLE; STAR FRUIT; SOYBEAN

Female Intimate Hygiene Antibacterial Gels

Female Intimate Hygiene Antibacterial Gels

Active Ingredient(s)

Benzalkonium bromide 0.10% w/w. Purpose: Antibiotic

Purpose

Antibiotic, Female Intimate Hygiene Antibacterial Gels

Use

for vagina to inhibit Staphylococcus aureus, Escherichia coli and Candida albicans.This product is not a substitute for medicines.

Warnings

For external use only
Disposable, do not reuse it

Do not use

- during menstruation, pregnancy, or breastfeeding

WHEN USING

do not get into eyes
if contact occurs, rinse eyes throughly with water

Stop use and ask a doctor if irritation or rash occurs. These may be signs of a serious condition.

Keep out of reach of children. If swallowed, get medical help or contact a Poison Control Center right away.

Directions

- Wash hands and clean the vulva
- Remove the front cover of the gel and insert the removed front cover into the rear end of the gel tube as a push rod
- Lie on your back and push the gel into the vagina with the gel pusher
- Take out the gel pusher, and lie still for three minutes.

Other information

- Store between 15-30C (59-86F)
- Avoid freezing and excessive heat above 40C (104F)

Inactive ingredients

Sophora Flavescens Root Extract, Averrhoa Carambola Fruit
Extract, Glycine Max (Soybean) Seed Extract, Pyrus Pyrifolia Fruit Extract